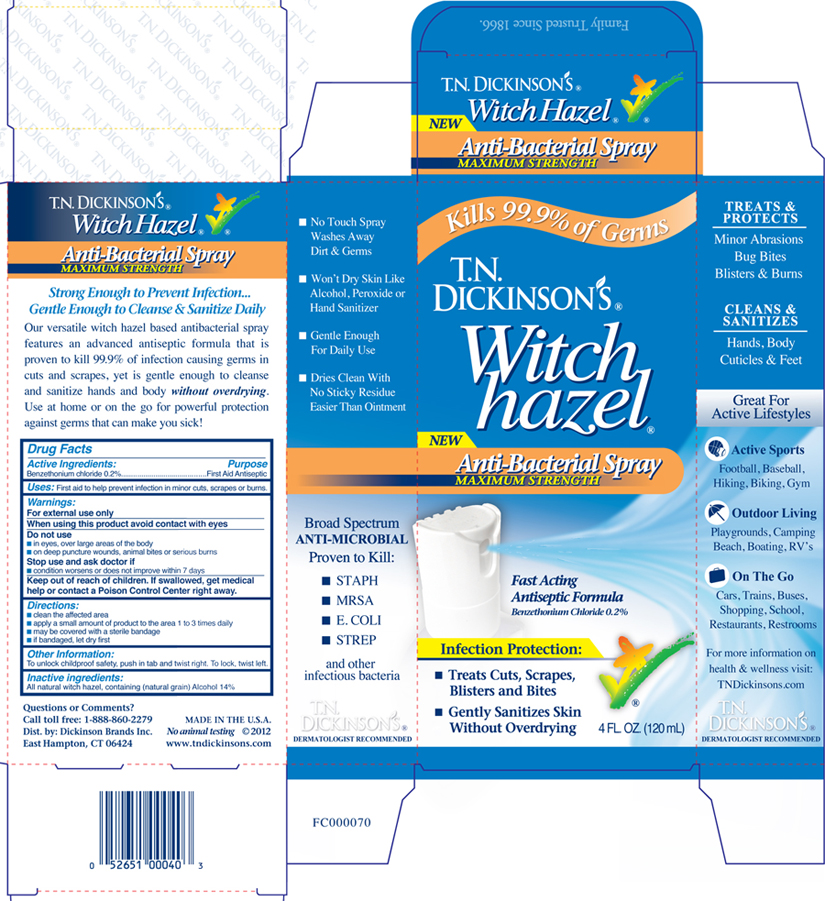 DRUG LABEL: TN Dickinsons Witch Hazel Antibacterial
NDC: 52651-006 | Form: SPRAY
Manufacturer: Dickinson Brands Inc.
Category: otc | Type: HUMAN OTC DRUG LABEL
Date: 20121009

ACTIVE INGREDIENTS: benzethonium chloride 2 mg/1 mL
INACTIVE INGREDIENTS: witch hazel

Drug Facts

Active ingredient
Benzethonium chloride .2%

Purpose

First Aid Antiseptic

Uses

First aid to help prevent infection in minor cuts scrapes or burns.

Warnings:

For external use only

When using this product avoid contact with eyes

Do not use

- in eyes, over large areas of the body
- on deep puncture wounds, animal bites or serious burns

Stop use and ask doctor if

- condition worsens or does not improve within 7 days

Keep out of reach of children. If swallowed, get medical
help or contact Poison Control Center right away.

Directions:

- clean the affected area
- apply a small amount of product to the area 1 to 3 times daily
- may be covered with a sterile bandage
- if bandaged, let dry first

Inactive ingredients:

All natural witch hazel, containing (natural grain) Alcohol 14%

Questions or Comments?
Call toll free: 1-888-860-2279
Dist. by: Dickinson Brands Inc.
East Hampton, CT 06424
MADE IN THE U.S.A.
www.tndickinsons.com
No animal testing

Product Packaging

The labels shown below represent a sample of that currently in use. Additional packaging may also be available.

Kills 99.9% of Germs

T.N. DICKINSON'S Witch hazel

Anti-Bacterial Spray
MAXIMUM STRENGTH

Fast Acting
Antiseptic Formula
Benzethonium Chloride 0.2%

Infection Protection:

- Treats Cuts, Scrapes, Blisters and Bites
- Gently Sanitizes Skin Without Overdrying